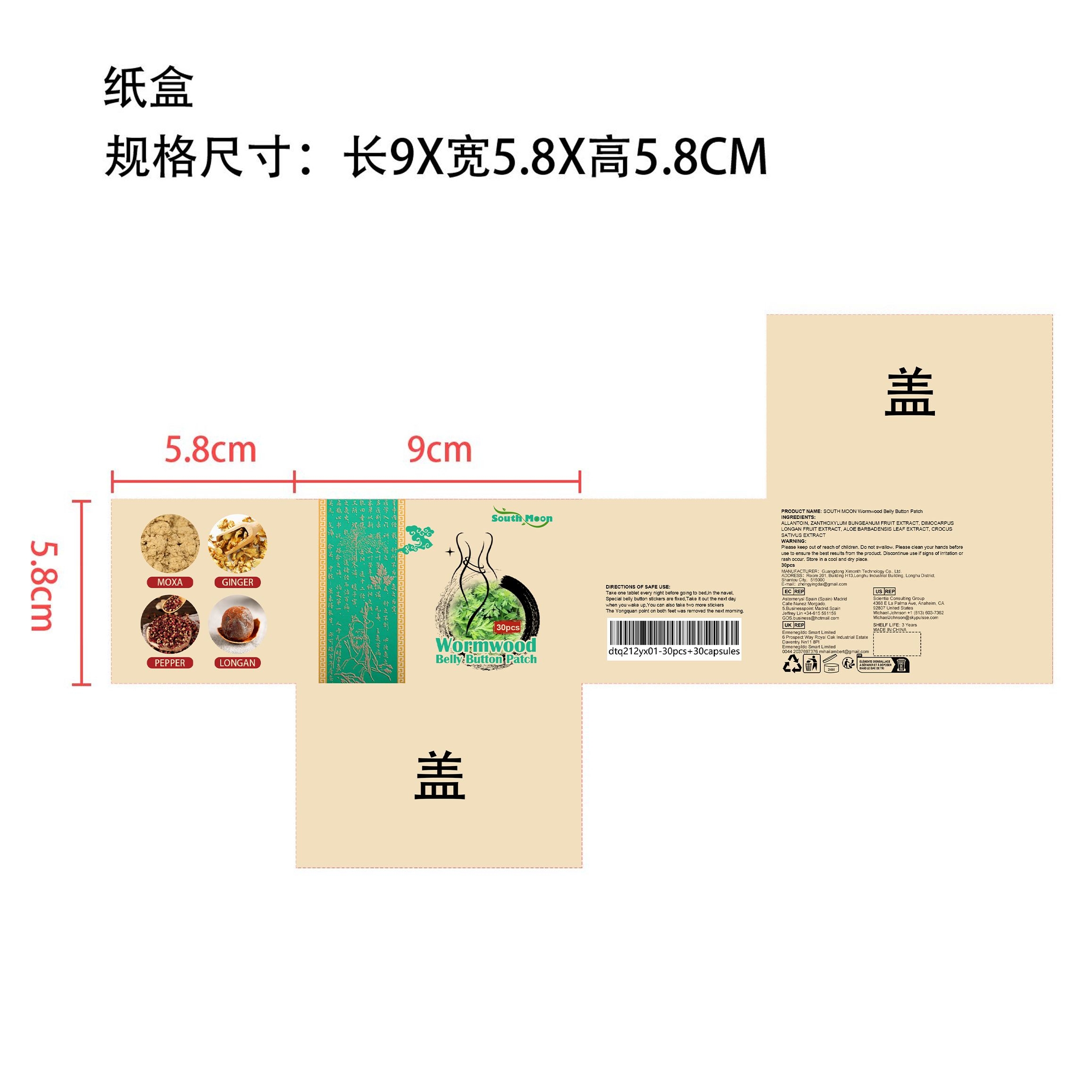 DRUG LABEL: Wormwood Belly Button Patch
NDC: 84660-009 | Form: PATCH
Manufacturer: Guangdong Ximonth Technology Co., Ltd.
Category: otc | Type: HUMAN OTC DRUG LABEL
Date: 20240905

ACTIVE INGREDIENTS: ALOE VERA LEAF 9.9 g/66 g; ZANTHOXYLUM BUNGEANUM FRUIT 16.5 g/66 g; SAFFRON 9.9 g/66 g; DIMOCARPUS LONGAN FRUIT 13.2 g/66 g
INACTIVE INGREDIENTS: ALLANTOIN 16.5 g/66 g

Active Ingredient(s)

ZANTHOXYLUM BUNGEANUM FRUIT EXTRACT、DIMOCARPUS LONGAN FRUIT EXTRACT、ALOE BARBADENSIS LEAF EXTRACT、 CROCUS SATIVUS EXTRACT

Purpose

Enhance firmness, shape the body

Use

Take one tablet every night before going to bed,in the navel, Special belly button stickers are fixed,Take it out the next day when you wake up,You can also take two more stickers The Yongquan point on both feet was removed the next morning.

Do not use

Discontinue use if signs of irritation or rash occur.

KEEP OUT OF REACH OF CHILDREN

Please keep out of reach of children. Do not swallow.

STORAGE AND HANDLING

Avoid freezing and excessive heat above 40C (104F) ）

Store in a cool and dry place.

INACTIVE INGREDIENT

ALLANTOIN